DRUG LABEL: Unknown
Manufacturer: Alcon
Category: prescription | Type: Human Prescription Drug Label
Date: 20060512

Statrol®
neomycin and polymyxin B
sulfates ophthalmic solution, USP

DESCRIPTION

STATROL® (Neomycin and Polymyxin B Sulfates Ophthalmic Solution, USP) is a sterile ophthalmic drug combining two antibacterials in solution form.

Each mL of solution contains: Active: Neomycin Sulfate equivalent to 3.5 mg Neomycin base, Polymyxin B Sulfate equal to 16,250 polymyxin B units.

Preservative: Benzalkonium Chloride .004%. Vehicle: 0.5% Hydroxypropyl Methylcellulose 2910. Inactive: Boric Acid, Sodium Chloride, Hydrochloric Acid and/or Sodium Hydroxide (to adjust pH), Purified Water. DM-02

CLINICAL PHARMACOLOGY

The anti-infective components in STATROL Ophthalmic Solution provide action against specific organisms susceptible to them. Polymyxin B Sulfate and Neomycin Sulfate are active in vitro against Staphylococcus aureus, Escherichia coli, Klebsiella/Enterobacter species, Neisseria species, Pseudomonas aeruginosa. This product does not provide adequate coverage against: Serratia marcescens, Streptococci, including Streptococcus pneumoniae.

INDICATIONS AND USAGE

STRATOL Ophthalmic Solution is indicated in the topical treatment of infections of the external eye and its adnexa caused by susceptible bacteria. Such infections encompass conjunctivitis, keratitis, and keratoconjunctivitis, blepharitis and blepharoconjunctivitis, acute meibomianitis and dacryocystitis.

CONTRAINDICATIONS

Epithelial herpes simplex keratitis (dendritic keratitis), vaccinia, varicella, and many other viral diseases of the cornea and conjunctiva. Mycobacterial infection of the eye. Fungal diseases of ocular structures. Hypersensitivity to a component of the medication.

WARNINGS

NOT FOR INJECTION INTO THE EYE. Should a sensitivity reaction occur, discontinue use. Neomycin Sulfate may cause cutaneous sensitization. Remove contact lenses before using.

PRECAUTIONS

General

As with other antibiotic preparations, prolonged use may result in overgrowth of nonsusceptible organisms, including fungi. If superinfection occurs, appropriate measures should be initiated. Whenever clinical judgment dictates; the patient should be examined with the aid of magnification, such as slit lamp biomicroscopy, and, where appropriate, corneal staining.

Information for patients

This product is sterile when packaged. To prevent contamination, care should be taken to avoid touching the bottle tip to eyelids or to any other surface. The use of this bottle by more than one person may spread infection. Keep bottle tightly closed when not in use. Keep out of the reach of children.

Carcinogenesis, Mutagenesis, Impairment of Fertility

Long-term studies in animals to evaluate carcinogenic or mutagenic potential have not been conducted with Polymyxin B Sulfate. Treatment of cultured human lymphocytes in-vitro with neomycin increased the frequency of chromosome aberrations at the highest concentrations (80 µg/mL) tested; however, the effects of neomycin on carcinogenesis and mutagenesis in humans are unknown.

Polymyxin B Sulfate has been reported to impair the motility of equine sperm, but its effects on male or female fertility are unknown.

Pregnancy

Teratogenic Effects

Pregnancy Category C. Animal reproduction studies have not been conducted with STATROL® (Neomycin and Polymyxin B Sulfates Ophthalmic Solution, USP). It is also not known whether Neomycin Sulfate and/or Polymyxin B Sulfate can cause fetal harm when administered to a pregnant woman or can affect reproduction capacity. STATROL Ophthalmic Solution should be given to a pregnant woman only if clearly needed.

Nursing Mothers

It is not known whether these drugs are excreted in human milk. Because many drugs are excreted in human milk, caution should be exercised when STATROL Ophthalmic Solution is administered to a nursing mother.

ADVERSE REACTIONS

Adverse reactions have occurred with the anti-infective components. Exact incidence figures are not available since no denominator of treated patients is available. Reactions occurring most often from the presence of the anti-infective ingredients are allergic sensitizations. (SEE WARNINGS.)

DOSAGE AND ADMINISTRATION

Instill one or two drops in the lower conjunctival sac(s) three or more times daily as required.

HOW SUPPLIED

STATROL (Neomycin and Polymyxin B Sulfates Ophthalmic Solution, USP) in 5 mL plastic DROP-TAINER® dispenser: NDC 0998-0623-05.

STORAGE: Store at 46° - 80°F (8° - 27°C).

Federal (USA) law prohibits dispensing without prescription.

Alcon®
OPHTHALMIC
ALCON (Puerto Rico) INC.
Humacao, Puerto Rico 00791 USA

Revised: June 1995
Printed in USA
238382